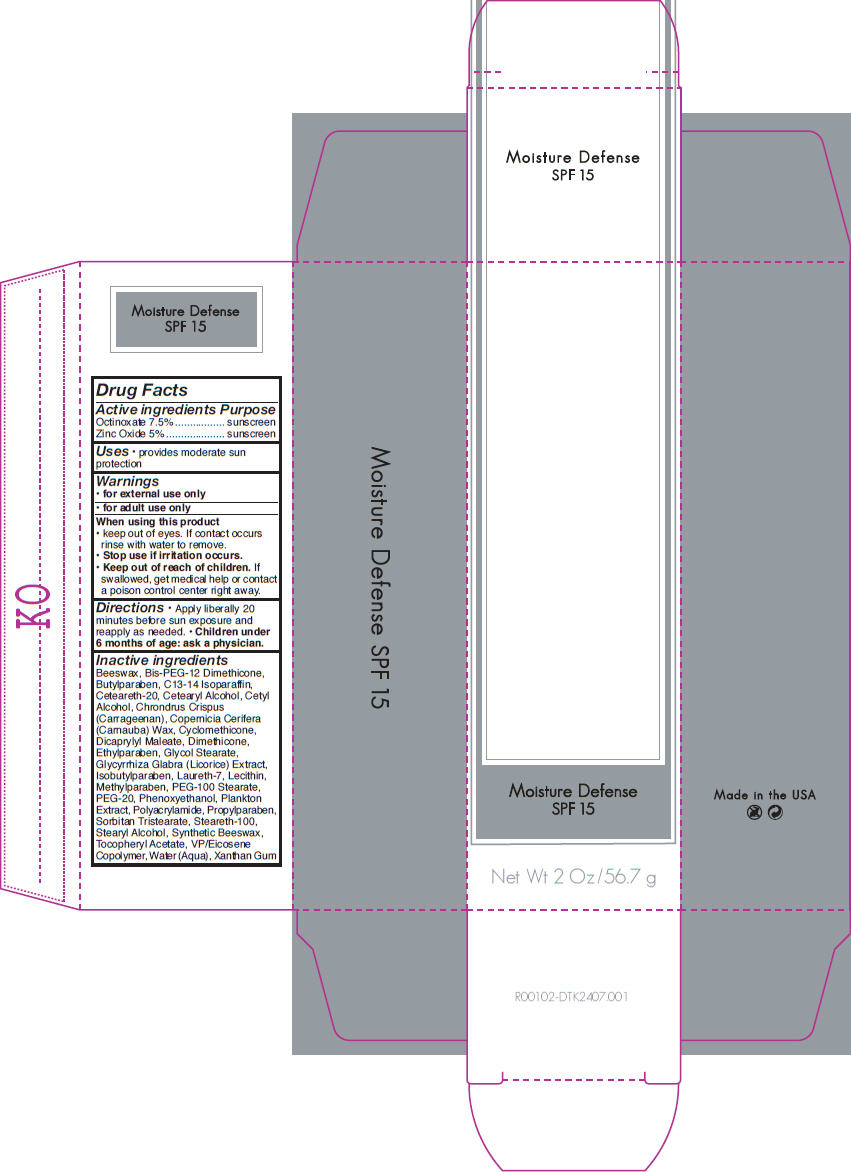 DRUG LABEL: Advanced Protection 
NDC: 24623-001 | Form: CREAM
Manufacturer: CBI Laboratories, Inc
Category: otc | Type: HUMAN OTC DRUG LABEL
Date: 20110105

ACTIVE INGREDIENTS: OCTINOXATE 0.075 g/1 g; Zinc Oxide 0.05 g/1 g
INACTIVE INGREDIENTS: XANTHAN GUM; CYCLOMETHICONE; CETYL ALCOHOL; DIOCTYL MALEATE; WATER; STEARYL ALCOHOL; GLYCOL STEARATE; ALPHA-TOCOPHEROL ACETATE; GLYCYRRHIZA GLABRA; CETOSTEARYL ALCOHOL; CHONDRUS CRISPUS

Moisture Defense
SPF 15

Drug Facts

ACTIVE INGREDIENT

Active ingredients | Purpose
Octinoxate 7.5% | sunscreen
Zinc Oxide 5% | sunscreen

Uses

- provides moderate sun protection

Warnings

- for external use only
- for adult use only

When using this product

- keep out of eyes. If contact occurs rinse with water to remove.

- Stop use if irritation occurs.

- Keep out of reach of children. If swallowed, get medical help or contact a poison control center right away.

Directions

- Apply liberally 20 minutes before sun exposure and reapply as needed.
- Children under 6 months of age: ask a physician.

Inactive ingredients

Beeswax, Bis-PEG-12 Dimethicone, Butylparaben, C13-14 Isoparaffin, Ceteareth-20, Cetearyl Alcohol, Cetyl Alcohol, Chrondrus Crispus (Carrageenan), Copernicia Cerifera (Carnauba) Wax, Cyclomethicone, Dicaprylyl Maleate, Dimethicone, Ethylparaben, Glycol Stearate, Glycyrrhiza Glabra (Licorice) Extract, Isobutylparaben, Laureth-7, Lecithin, Methylparaben, PEG-100 Stearate, PEG-20, Phenoxyethanol, Plankton Extract, Polyacrylamide, Propylparaben, Sorbitan Tristearate, Steareth-100, Stearyl Alcohol, Synthetic Beeswax, Tocopheryl Acetate, VP/Eicosene Copolymer, Water (Aqua), Xanthan Gum

PRINCIPAL DISPLAY PANEL - 56.7 g Carton

Moisture Defense
SPF 15

Net Wt 2 Oz/56.7 g